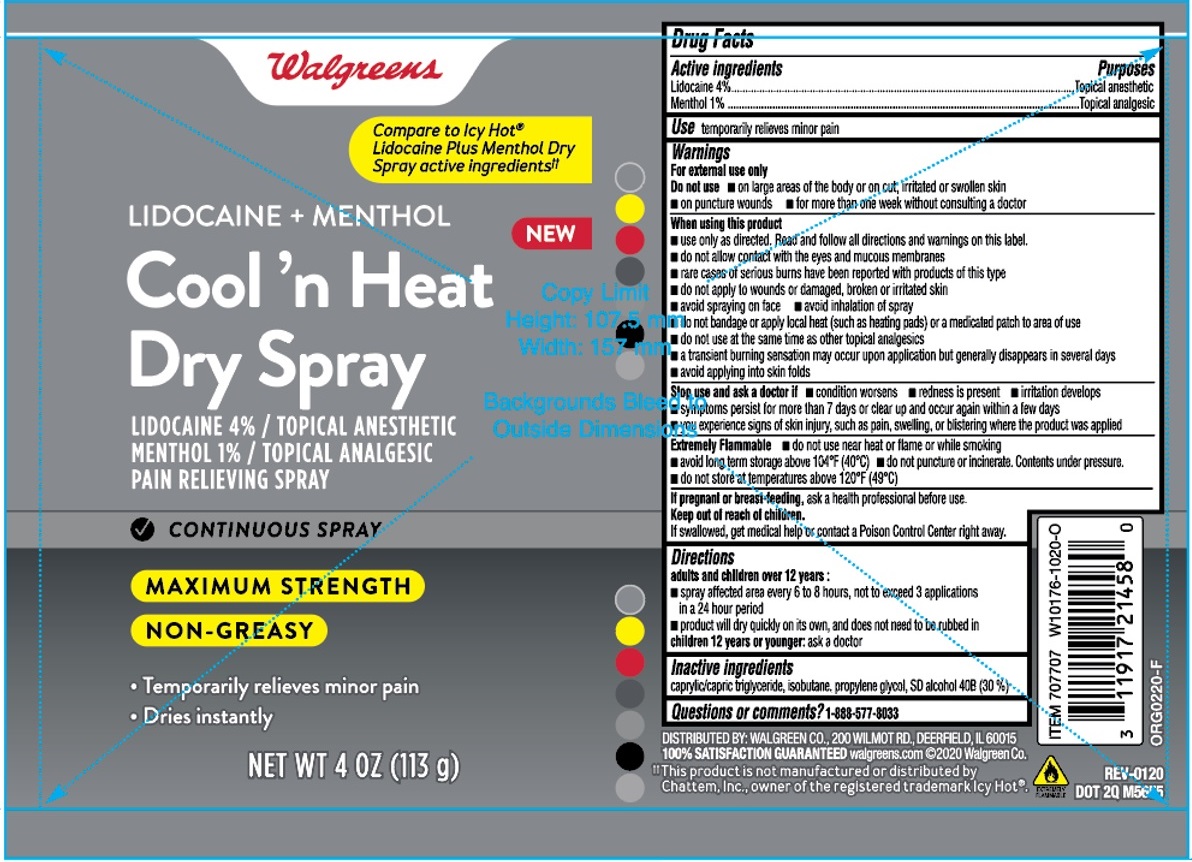 DRUG LABEL: Walgreens Cool N Heat Dry
NDC: 0363-9670 | Form: AEROSOL, SPRAY
Manufacturer: Walgreens Co
Category: otc | Type: HUMAN OTC DRUG LABEL
Date: 20210810

ACTIVE INGREDIENTS: LIDOCAINE 4 g/100 g; MENTHOL, UNSPECIFIED FORM 1 g/100 g
INACTIVE INGREDIENTS: MEDIUM-CHAIN TRIGLYCERIDES; ISOBUTANE; PROPYLENE GLYCOL; ALCOHOL

Walgreens Cool 'n Heat Dry Spray

Active ingredients

Lidocaine 4%

Menthol 1%

Purposes

Topical anesthetic

Topical analgesic

Use

temporarily relieves minor pain

Warnings

For external use only

Do not use • on large areas of the body or on cut, irritated or swollen skin
• on puncture wounds • for more than one week without consulting a doctor

When using this product
• use only as directed. Read and follow all directions and warnings on this label.
• do not allow contact with the eyes and mucous membranes
• rare cases of serious burns have been reported with products of this type
• do not apply to wounds or damaged, broken or irritated skin
• avoid spraying on face • avoid inhalation of spray
• do not bandage or apply local heat (such as heating pads) or a medicated patch to area of use
• do not use at the same time as other topical analgesics
• a transient burning sensation may occur upon application but generally disappears in several days
• avoid applying into skin folds

Stop use and ask a doctor if • condition worsens • redness is present • irritation develops
• symptoms persist for more than 7 days or clear up and occur again within a few days
• you experience signs of skin injury, such as pain, swelling, or blistering where the product was applied

Extremely Flammable • do not use near heat or flame or while smoking
• avoid long term storage above 104°F (40°C) • do not puncture or incinerate. Contents under pressure.
• do not store at temperatures above 120°F (49°C)

If pregnant or breast-feeding, ask a health professional before use.

Keep out of reach of children.
If swallowed, get medical help or contact a Poison Control Center right away.

Directions

adults and children over 12 years:
• spray affected area every 6 to 8 hours, not to exceed 3 applications in a 24 hour period
• product will dry quickly on its own, and does not need to be rubbed in

children 12 years or younger: ask a doctor

Inactive ingredients

caprylic/capric triglyceride, isobutane, propylene glycol, SD alcohol 40B (30%)

Compare to Icy Hot® Lidocaine Plus Menthol Dry Spray active ingredients††

PAIN RELIEVING SPRAY

• CONTINUOUS SPRAY

MAXIMUM STRENGTH

NON - GREASY

• Temporarily relieves minor pain

• Dries instantly

DISTRIBUTED BY: WALGREEN CO., 200 WILMOT RD., DEERFIELD, IL 60015

100% SATISFACTION GUARANTEED walgreens.com©2020 Walgreen Co.

††This product is not manufactured or distributed by Chattem, Inc., owner of the registered trademark Icy Hot®.